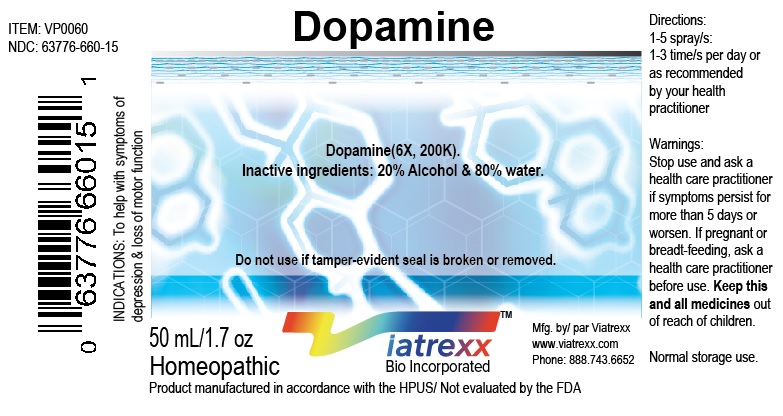 DRUG LABEL: Dopamine
NDC: 63776-660 | Form: SPRAY
Manufacturer: VIATREXX BIO INCORPORATED
Category: homeopathic | Type: HUMAN OTC DRUG LABEL
Date: 20180111

ACTIVE INGREDIENTS: Dopamine 200 [kp_C]/1 mL
INACTIVE INGREDIENTS: Alcohol; Water

Active Ingredients

Dopamine, 6X, 200K

Purpose:

Dopamine | neurological support

Uses

To help with dopamine support

Warnings

Stop use and ask a health care practitioner if symptoms persist for more than five days or worsen. If pregnant or breastfeeding, ask a health care practitioner before use.

Dosage

1-3 spray(s); 1-3 time(s) per day or as recommended by your health care practitioner.

KEEP OUT OF REACH OF CHILDREN

Keep this and all medicines out of reach of children.

Other Ingredients

20% Alcohol and 80% Water

Other Information

Normal storage use.
Do not use if tamper-evident seal is broken or removed.

Questions

info@viatrexx.com

Principal Display Panel

ITEM: VP0060
NDC 63776-660-14
Homeopathic remedy
Dopamine
• To help with dopamine support
Oral spray
30ml 1 oz
Viatrexx™ Bio Incorporated
Manufactured by Viatrexx
www.viatrexx.com
Newark, DE 19713

Dopamine
50 ml
1.7 oz
Viatrexx™ Bio Incorporated
ITEM: VP0060
NDC: 63776-660-15
INDICATIONS:
To help with dopamine support
DIRECTIONS:
1-3 spray(s); 1-3 time(s) per day or as recommended by your health care practitioner.
Mfg. for
Viatrexx Bio Incorporated.
www.viatrexx.com
Newark, DE 19713